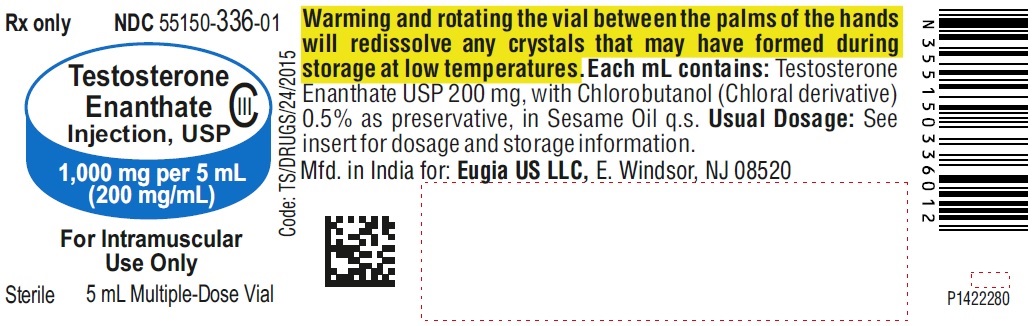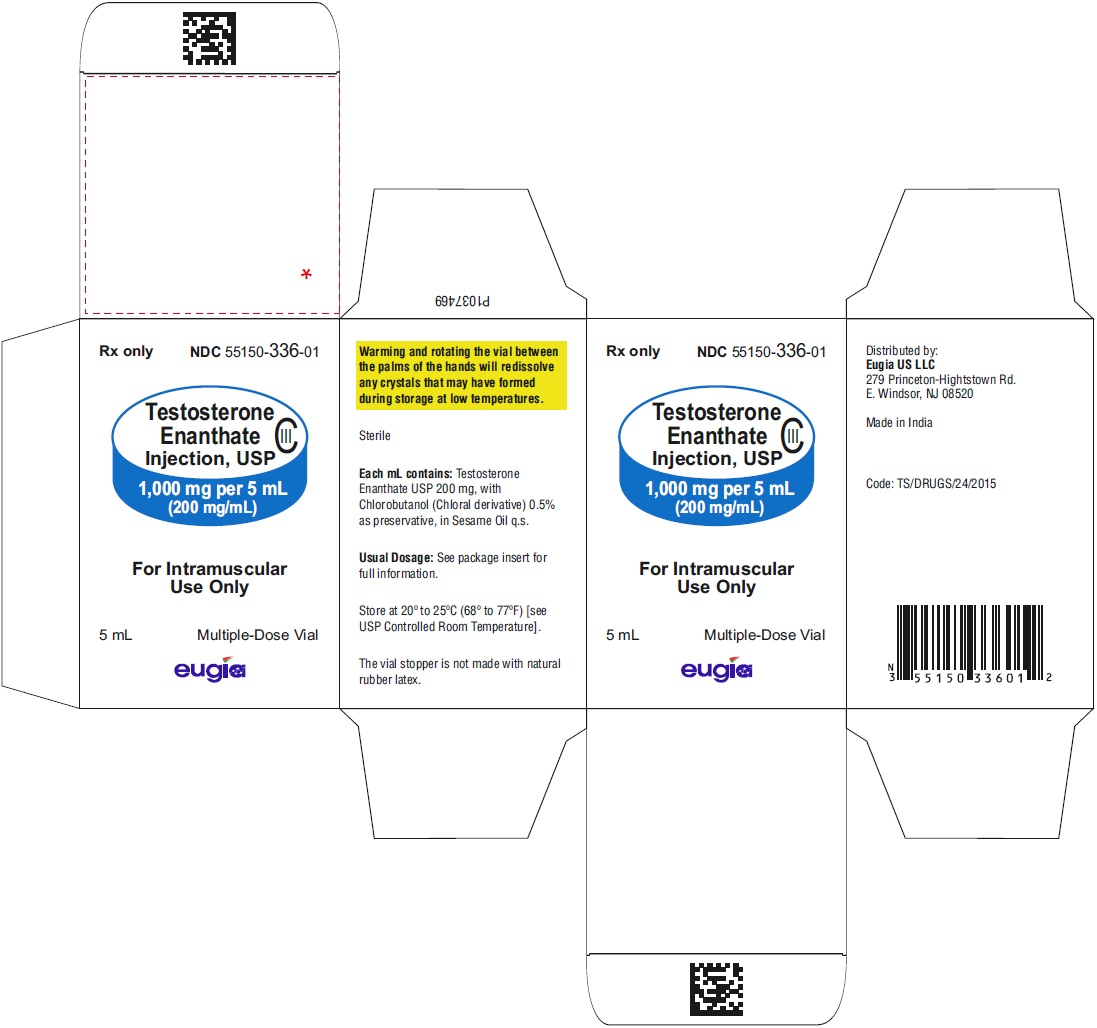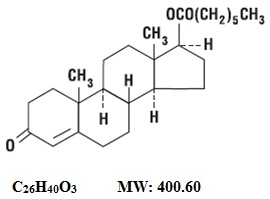 DRUG LABEL: TESTOSTERONE ENANTHATE
NDC: 55150-336 | Form: INJECTION, SOLUTION
Manufacturer: Eugia US LLC
Category: prescription | Type: Human Prescription Drug Label
Date: 20250716
DEA Schedule: CIII

ACTIVE INGREDIENTS: TESTOSTERONE ENANTHATE 200 mg/1 mL
INACTIVE INGREDIENTS: SESAME OIL; CHLOROBUTANOL

Testosterone Enanthate Injection, USP CIII
Rx only
Multiple Dose Vial

DESCRIPTION

Testosterone enanthate injection, USP provides testosterone enanthate, a derivative of the primary endogenous androgen testosterone, for intramuscular administration. In their active form, androgens have a 17-beta-hydroxy group. Esterification of the 17-beta-hydroxy group increases the duration of action of testosterone; hydrolysis to free testosterone occurs in vivo. Each mL of sterile, clear colorless to pale yellow color oily solution provides 200 mg testosterone enanthate, USP in sesame oil with 5 mg chlorobutanol (chloral derivative) as a preservative.
Testosterone enanthate is designated chemically as androst-4-en-3-one, 17-[(1-oxoheptyl)-oxy]-, (17β)-. Structural formula:

CLINICAL PHARMACOLOGY

Endogenous androgens are responsible for the normal growth and development of the male sex organs and for maintenance of secondary sex characteristics. These effects include growth and maturation of prostate, seminal vesicles, penis, and scrotum; development of male hair distribution, such as beard, pubic, chest, and axillary hair; laryngeal enlargement; vocal cord thickening; alterations in body musculature; and fat distribution.
Androgens also cause retention of nitrogen, sodium, potassium, and phosphorus, and decreased urinary excretion of calcium. Androgens have been reported to increase protein anabolism and decrease protein catabolism. Nitrogen balance is improved only when there is sufficient intake of calories and protein.
Androgens are responsible for the growth spurt of adolescence and for the eventual termination of linear growth which is brought about by fusion of the epiphyseal growth centers. In children, exogenous androgens accelerate linear growth rates but may cause a disproportionate advancement in bone maturation. Use over long periods may result in fusion of the epiphyseal growth centers and termination of the growth process. Androgens have been reported to stimulate the production of red blood cells by enhancing the production of erythropoietic stimulating factor.
During exogenous administration of androgens, endogenous testosterone release is inhibited through feedback inhibition of pituitary luteinizing hormone (LH). At large doses of exogenous androgens, spermatogenesis may also be suppressed through feedback inhibition of pituitary follicle stimulating hormone (FSH).
There is a lack of substantial evidence that androgens are effective in fractures, surgery, convalescence, and functional uterine bleeding.

PHARMACOKINETICS

Testosterone esters are less polar than free testosterone. Testosterone esters in oil injected intramuscularly are absorbed slowly from the lipid phase; thus testosterone enanthate can be given at intervals of two to four weeks.
Testosterone in plasma is 98 percent bound to a specific testosterone-estradiol binding globulin, and about two percent is free. Generally, the amount of this sex-hormone binding globulin (SHBG) in the plasma will determine the distribution of testosterone between free and bound forms, and the free testosterone concentration will determine its half-life.
About 90 percent of a dose of testosterone is excreted in the urine as glucuronic and sulfuric acid conjugates of testosterone and its metabolites; about six percent of a dose is excreted in the feces, mostly in the unconjugated form. Inactivation of testosterone occurs primarily in the liver. Testosterone is metabolized to various 17-keto steroids through two different pathways. There are considerable variations of the half-life of testosterone as reported in the literature, ranging from 10 to 100 minutes.
In responsive tissues, the activity of testosterone appears to depend on reduction to dihydrotestosterone (DHT), which binds to cytosol receptor proteins. The steroid-receptor complex is transported to the nucleus where it initiates transcription events and cellular changes related to androgen action.

INDICATIONS AND USAGE

Males
Testosterone enanthate injection is indicated for replacement therapy in conditions associated with a deficiency or absence of endogenous testosterone.
Primary hypogonadism (congenital or acquired) – Testicular failure due to cryptorchidism, bilateral torsion, orchitis, vanishing testis syndrome, or orchidectomy.
Hypogonadotropic hypogonadism (congenital or acquired) – Gonadotropin or luteinizing hormone-releasing hormone (LHRH) deficiency, or pituitary-hypothalamic injury from tumors, trauma, or radiation. (Appropriate adrenal cortical and thyroid hormone replacement therapy are still necessary, however, and are actually of primary importance.)
If the above conditions occur prior to puberty, androgen replacement therapy will be needed during the adolescent years for development of secondary sexual characteristics. Prolonged androgen treatment will be required to maintain sexual characteristics in these and other males who develop testosterone deficiency after puberty.
Safety and efficacy of testosterone enanthate injection in men with age-related hypogonadism have not been established.
Delayed puberty – Testosterone enanthate injection may be used to stimulate puberty in carefully selected males with clearly delayed puberty. These patients usually have a familial pattern of delayed puberty that is not secondary to a pathological disorder; puberty is expected to occur spontaneously at a relatively late date. Brief treatment with conservative doses may occasionally be justified in these patients if they do not respond to psychological support. The potential adverse effect on bone maturation should be discussed with the patient and parents prior to androgen administration. An X-ray of the hand and wrist to determine bone age should be obtained every six months to assess the effect of treatment on the epiphyseal centers (see WARNINGS).
Females
Metastatic mammary cancer – Testosterone enanthate injection may be used secondarily in women with advancing inoperable metastatic (skeletal) mammary cancer who are one to five years postmenopausal. Primary goals of therapy in these women include ablation of the ovaries. Other methods of counteracting estrogen activity are adrenalectomy, hypophysectomy, and/or antiestrogen therapy. This treatment has also been used in premenopausal women with breast cancer who have benefited from oophorectomy and are considered to have a hormone-responsive tumor. Judgment concerning androgen therapy should be made by an oncologist with expertise in this field.

CONTRAINDICATIONS

Androgens are contraindicated in men with carcinomas of the breast or with known or suspected carcinomas of the prostate and in women who are or may become pregnant. When administered to pregnant women, androgens cause virilization of the external genitalia of the female fetus. This virilization includes clitoromegaly, abnormal vaginal development, and fusion of genital folds to form a scrotal-like structure. The degree of masculinization is related to the amount of drug given and the age of the fetus and is most likely to occur in the female fetus when the drugs are given in the first trimester. If the patient becomes pregnant while taking androgens, she should be apprised of the potential hazard to the fetus.
This preparation is also contraindicated in patients with a history of hypersensitivity to any of its components.

WARNINGS

In patients with breast cancer and in immobilized patients, androgen therapy may cause hypercalcemia by stimulating osteolysis. In patients with cancer, hypercalcemia may indicate progression of bony metastasis. If hypercalcemia occurs, the drug should be discontinued and appropriate measures instituted.
Prolonged use of high doses of androgens has been associated with the development of peliosis hepatis and hepatic neoplasms including hepatocellular carcinoma (see PRECAUTIONS, Carcinogenesis). Peliosis hepatis can be a life-threatening or fatal complication.
If cholestatic hepatitis with jaundice appears or if liver function tests become abnormal, the androgen should be discontinued and the etiology should be determined. Drug-induced jaundice is reversible when the medication is discontinued.
Geriatric patients treated with androgens may be at an increased risk for the development of prostatic hypertrophy and prostatic carcinoma.
There have been postmarketing reports of venous thromboembolic events, including deep vein thrombosis (DVT) and pulmonary embolism (PE), in patients using testosterone products, such as testosterone enanthate. Evaluate patients who report symptoms of pain, edema, warmth and erythema in the lower extremity for DVT and those who present with acute shortness of breath for PE. If a venous thromboembolic event is suspected, discontinue treatment with testosterone enanthate and initiate appropriate workup and management.
Long term clinical safety trials have not been conducted to assess the cardiovascular outcomes of testosterone replacement therapy in men. To date, epidemiologic studies and randomized controlled trials have been inconclusive for determining the risk of major adverse cardiovascular events (MACE), such as non-fatal myocardial infarction, non-fatal stroke, and cardiovascular death, with the use of testosterone compared to non-use. Some studies, but not all, have reported an increased risk of MACE in association with use of testosterone replacement therapy in men. Patients should be informed of this possible risk when deciding whether to use or to continue to use testosterone enanthate.

Testosterone can increase blood pressure which can increase cardiovascular (CV) risk over time. Monitor blood pressure periodically in men using testosterone products, especially in men with hypertension. Testosterone products are not recommended for use in patients with uncontrolled hypertension.

Testosterone has been subject to abuse, typically at doses higher than recommended for the approved indication and in combination with other anabolic steroids. Anabolic androgenic steroid abuse can lead to serious cardiovascular and psychiatric adverse reactions (see DRUG ABUSE AND DEPENDENCE).
If testosterone abuse is suspected, check serum testosterone concentrations to ensure they are within therapeutic range. However, testosterone levels may be in the normal or subnormal range in men abusing synthetic testosterone derivatives. Counsel patients concerning the serious adverse reactions associated with abuse of testosterone and anabolic steroids. Conversely, consider the possibility of testosterone and anabolic steroid abuse in suspected patients who present with serious cardiovascular or psychiatric adverse events.
Due to sodium and water retention, edema with or without congestive heart failure may be a serious complication in patients with preexisting cardiac, renal, or hepatic disease. In addition to discontinuation of the drug, diuretic therapy may be required. If the administration of testosterone enanthate is restarted, a lower dose should be used.
Gynecomastia frequently develops and occasionally persists in patients being treated for hypogonadism.
Androgen therapy should be used cautiously in healthy males with delayed puberty. The effect on bone maturation should be monitored by assessing bone age of the wrist and hand every six months. In children, androgen treatment may accelerate bone maturation without producing compensatory gain in linear growth. This adverse effect may result in compromised adult stature. The younger the child the greater the risk of compromising final mature height.

PRECAUTIONS

General

Women should be observed for signs of virilization (deepening of the voice, hirsutism, acne, clitoromegaly, and menstrual irregularities). Discontinuation of drug therapy at the time of evidence of mild virilism is necessary to prevent irreversible virilization. Such virilization is usual following androgen use at high doses and is not prevented by concomitant use of estrogens. A decision may be made by the patient and the physician that some virilization will be tolerated during treatment for breast carcinoma.
Because androgens may alter serum cholesterol concentration, caution should be used when administering these drugs to patients with a history of myocardial infarction or coronary artery disease. Serial determinations of serum cholesterol should be made and therapy adjusted accordingly. A causal relationship between myocardial infarction and hypercholesterolemia has not been established.

Information for Patients

Male adolescent patients receiving androgens for delayed puberty should have bone development checked every six months.
The physician should instruct patients to report any of the following side effects of androgens:
Adult or adolescent males – too frequent or persistent erections of the penis.
Women – hoarseness, acne, changes in menstrual periods, or more facial hair.
All patients – any nausea, vomiting, changes in skin color, or ankle swelling.

Geriatric Use

Clinical studies of testosterone enanthate did not include sufficient numbers of subjects, aged 65 and older, to determine whether they respond differently from younger subjects. Testosterone replacement is not indicated in geriatric patients who have age-related hypogonadism only (“andropause”), because there is insufficient safety and efficacy information to support such use. Current studies do not assess whether testosterone use increases risks of prostate cancer, prostate hyperplasia, and cardiovascular disease in the geriatric population.
Intramuscular Administration
When properly given, injections of testosterone enanthate are well tolerated. Care should be taken to slowly inject the preparation deeply into the gluteal muscle, being sure to follow the usual precautions for intramuscular administration, such as the avoidance of intravascular injection. There have been rare postmarketing reports of transient reactions involving urge to cough, coughing fits, and respiratory distress immediately after the injection of testosterone enanthate, an oil-based depot preparation (see DOSAGE AND ADMINISTRATION).

Laboratory Tests

Women with disseminated breast carcinoma should have frequent determination of urine and serum calcium levels during the course of androgen therapy (see WARNINGS).
Periodic (every six months) X-ray examinations of bone age should be made during treatment of pre-pubertal males to determine the rate of bone maturation and the effects of androgen therapy on the epiphyseal centers.
Hemoglobin and hematocrit should be checked periodically for polycythemia in patients who are receiving high doses of androgens.

Drug Interactions

When administered concurrently, the following drugs may interact with androgens:
Anticoagulants, oral – C-17 substituted derivatives of testosterone, such as methandrostenolone, have been reported to decrease the anticoagulant requirement. Patients receiving oral anticoagulant therapy require close monitoring especially when androgens are started or stopped.
Antidiabetic drugs and insulin – In diabetic patients, the metabolic effects of androgens may decrease blood glucose and insulin requirements.
ACTH and corticosteroids – Enhanced tendency toward edema. Use caution when giving these drugs together, especially in patients with hepatic or cardiac disease.
Oxyphenbutazone – Elevated serum levels of oxyphenbutazone may result.

Drug/Laboratory Test Interferences

Androgens may decrease levels of thyroxine-binding globulin, resulting in decreased total T4 serum levels and increased resin uptake of T3 and T4. Free thyroid hormone levels remain unchanged, however, and there is no clinical evidence of thyroid dysfunction.

Carcinogenesis

Testosterone has been tested by subcutaneous injection and implantation in mice and rats. The implant induced cervical-uterine tumors in mice, which metastasized in some cases. There is suggestive evidence that injection of testosterone into some strains of female mice increases their susceptibility to hepatoma. Testosterone is also known to increase the number of tumors and decrease the degree of differentiation of chemically induced carcinomas of the liver in rats.
There are rare reports of hepatocellular carcinoma in patients receiving long-term therapy with androgens in high doses. Withdrawal of the drugs did not lead to regression of the tumors in all cases.
Geriatric patients treated with androgens may be at an increased risk for the development of prostatic hypertrophy and prostatic carcinoma.

Pregnancy: Teratogenic Effects

(see CONTRAINDICATIONS).

Nursing Mothers

It is not known whether androgens are excreted in human milk. Because many drugs are excreted in human milk and because of the potential for serious adverse reactions in nursing infants from androgens, a decision should be made whether to discontinue nursing or to discontinue the drug, taking into account the importance of the drug to the mother.

Pediatric Use

Androgen therapy should be used very cautiously in pediatric patients and only by specialists who are aware of the adverse effects on bone maturation. Skeletal maturation must be monitored every six months by an X-ray of the hand and wrist (see INDICATIONS AND USAGE, and WARNINGS).

ADVERSE REACTIONS

Endocrine and Urogenital, Female – The most common side effects of androgen therapy are amenorrhea and other menstrual irregularities, inhibition of gonadotropin secretion, and virilization, including deepening of the voice and clitoral enlargement. The latter usually is not reversible after androgens are discontinued. When administered to a pregnant woman, androgens cause virilization of the external genitalia of the female fetus.
Male – Gynecomastia, and excessive frequency and duration of penile erections. Oligospermia may occur at high dosages (see CLINICAL PHARMACOLOGY).
Skin and Appendages – Hirsutism, male pattern baldness, and acne.
Cardiovascular Disorders – myocardial infarction, stroke
Fluid and Electrolyte Disturbances – Retention of sodium, chloride, water, potassium, calcium (see WARNINGS), and inorganic phosphates.
Gastrointestinal – Nausea, cholestatic jaundice, alterations in liver function tests; rarely, hepatocellular neoplasms, peliosis hepatis (see WARNINGS).
Hematologic – Suppression of clotting factors II, V, VII, and X; bleeding in patients on concomitant anticoagulant therapy; polycythemia.
Nervous System – Increased or decreased libido, headache, anxiety, depression, and generalized paresthesia.
Metabolic – Increased serum cholesterol.
Vascular Disorders – venous thromboembolism
Miscellaneous – Rarely, anaphylactoid reactions; inflammation and pain at injection site.

DRUG ABUSE AND DEPENDENCE

Controlled Substance

Testosterone enanthate injection contains testosterone, a Schedule III controlled substance in the Controlled Substances Act.

Abuse

Drug abuse is intentional non-therapeutic use of a drug, even once, for its rewarding psychological and physiological effects. Abuse and misuse of testosterone are seen in male and female adults and adolescents. Testosterone, often in combination with other anabolic androgenic steroids (AAS), and not obtained by prescription through a pharmacy, may be abused by athletes and bodybuilders. There have been reports of misuse of men taking higher doses of legally obtained testosterone than prescribed and continuing testosterone despite adverse events or against medical advice.
Abuse-Related Adverse Reactions
Serious adverse reactions have been reported in individuals who abuse anabolic androgenic steroids, and include cardiac arrest, myocardial infarction, hypertrophic cardiomyopathy, congestive heart failure, cerebrovascular accident, hepatotoxicity, and serious psychiatric manifestations, including major depression, mania, paranoia, psychosis, delusions, hallucinations, hostility and aggression.
The following adverse reactions have also been reported in men: transient ischemic attacks, convulsions, hypomania, irritability, dyslipidemias, testicular atrophy, subfertility, and infertility.
The following additional adverse reactions have been reported in women: hirsutism, virilization, deepening of voice, clitoral enlargement, breast atrophy, male-pattern baldness, and menstrual irregularities.
The following adverse reactions have been reported in male and female adolescents: premature closure of bony epiphyses with termination of growth, and precocious puberty.
Because these reactions are reported voluntarily from a population of uncertain size and may include abuse of other agents, it is not always possible to reliably estimate their frequency or establish a causal relationship to drug exposure.

Dependence

Behaviors Associated with Addiction
Continued abuse of testosterone and other anabolic steroids, leading to addiction is characterized by the following behaviors:

- Taking greater dosages than prescribed
- Continued drug use despite medical and social problems due to drug use
- Spending significant time to obtain the drug when supplies of the drug are interrupted
- Giving a higher priority to drug use than other obligations
- Having difficulty in discontinuing the drug despite desires and attempts to do so
- Experiencing withdrawal symptoms upon abrupt discontinuation of use

Physical dependence is characterized by withdrawal symptoms after abrupt drug discontinuation or a significant dose reduction of a drug. Individuals taking supratherapeutic doses of testosterone may experience withdrawal symptoms lasting for weeks or months which include depressed mood, major depression, fatigue, craving, restlessness, irritability, anorexia, insomnia, decreased libido and hypogonadotropic hypogonadism.
Drug dependence in individuals using approved doses of testosterone for approved indications has not been documented.

OVERDOSAGE

There have been no reports of acute overdosage with androgens.

DOSAGE AND ADMINISTRATION

Prior to initiating testosterone enanthate injection, confirm the diagnosis of hypogonadism by ensuring that serum testosterone concentrations have been measured in the morning in the morning on at least two separate days and that these serum testosterone concentrations are below the normal range.
Dosage and duration of therapy with testosterone enanthate injection will depend on age, sex, diagnosis, patient’s response to treatment, and appearance of adverse effects. When properly given, injections of testosterone enanthate are well tolerated. Care should be taken to slowly inject the preparation deeply into the gluteal muscle, being sure to follow the usual precautions for intramuscular administration, such as the avoidance of intravascular injection (see PRECAUTIONS).
In general, total doses above 400 mg per month are not required because of the prolonged action of the preparation. Injections more frequently than every two weeks are rarely indicated. NOTE: Use of a wet needle or wet syringe may cause the solution to become cloudy; however this does not affect the potency of the material. Parenteral drug products should be inspected visually for particulate matter and discoloration prior to administration, whenever solution and container permit. Testosterone enanthate injection is a clear, colorless to pale yellow color oily solution.
Male hypogonadism: As replacement therapy, i.e., for eunuchism, the suggested dosage is 50 to 400 mg every 2 to 4 weeks.
In males with delayed puberty: Various dosage regimens have been used; some call for lower dosages initially with gradual increases as puberty progresses, with or without a decrease to maintenance levels. Other regimens call for higher dosage to induce pubertal changes and lower dosage for maintenance after puberty. The chronological and skeletal ages must be taken into consideration, both in determining the initial dose and in adjusting the dose. Dosage is within the range of 50 to 200 mg every 2 to 4 weeks for a limited duration, for example, 4 to 6 months. X-rays should be taken at appropriate intervals to determine the amount of bone maturation and skeletal development (see INDICATIONS AND USAGE, and WARNINGS).
Palliation of inoperable mammary cancer in women: A dosage of 200 to 400 mg every 2 to 4 weeks is recommended. Women with metastatic breast carcinoma must be followed closely because androgen therapy occasionally appears to accelerate the disease.

HOW SUPPLIED

Testosterone enanthate injection, USP is a clear, colorless to pale yellow color oily solution and is supplied as follows:
1,000 mg per 5 mL (200 mg/mL)
5 mL multiple-dose vial NDC 55150-336-01
packaged individually
STORAGE
Testosterone enanthate injection, USP should be stored at 20º to 25ºC (68º to 77ºF) [see USP Controlled Room Temperature]. Warming and rotating the vial between the palms of the hands will redissolve any crystals that may have formed during storage at low temperatures.
For Prescription Use Only
The vial stopper is not made with natural rubber latex.
Distributed by:
Eugia US LLC
279 Princeton-Hightstown Rd.
E. Windsor, NJ 08520
Manufactured by:
Eugia Pharma Specialities Limited
Hyderabad - 500032
India
Medical Inquiries:
1-866-850-2876
Revised: July 2025

PACKAGE LABEL-PRINCIPAL DISPLAY PANEL - 1,000 mg per 5 mL (200 mg/mL) - Container Label

Rx only NDC 55150-336-01
Testosterone CIII
Enanthate
Injection, USP
1,000 mg per 5 mL
(200 mg/mL)
For Intramuscular
Use Only
Sterile 5 mL Multiple-Dose Vial

PACKAGE LABEL-PRINCIPAL DISPLAY PANEL - 1,000 mg per 5 mL (200 mg/mL) - Container-Carton (1 Vial)

Rx only NDC 55150-336-01
Testosterone CIII
Enanthate
Injection, USP
1,000 mg per 5 mL
(200 mg/mL)
For Intramuscular
Use Only
5 mL Multiple-Dose Vial
eugia